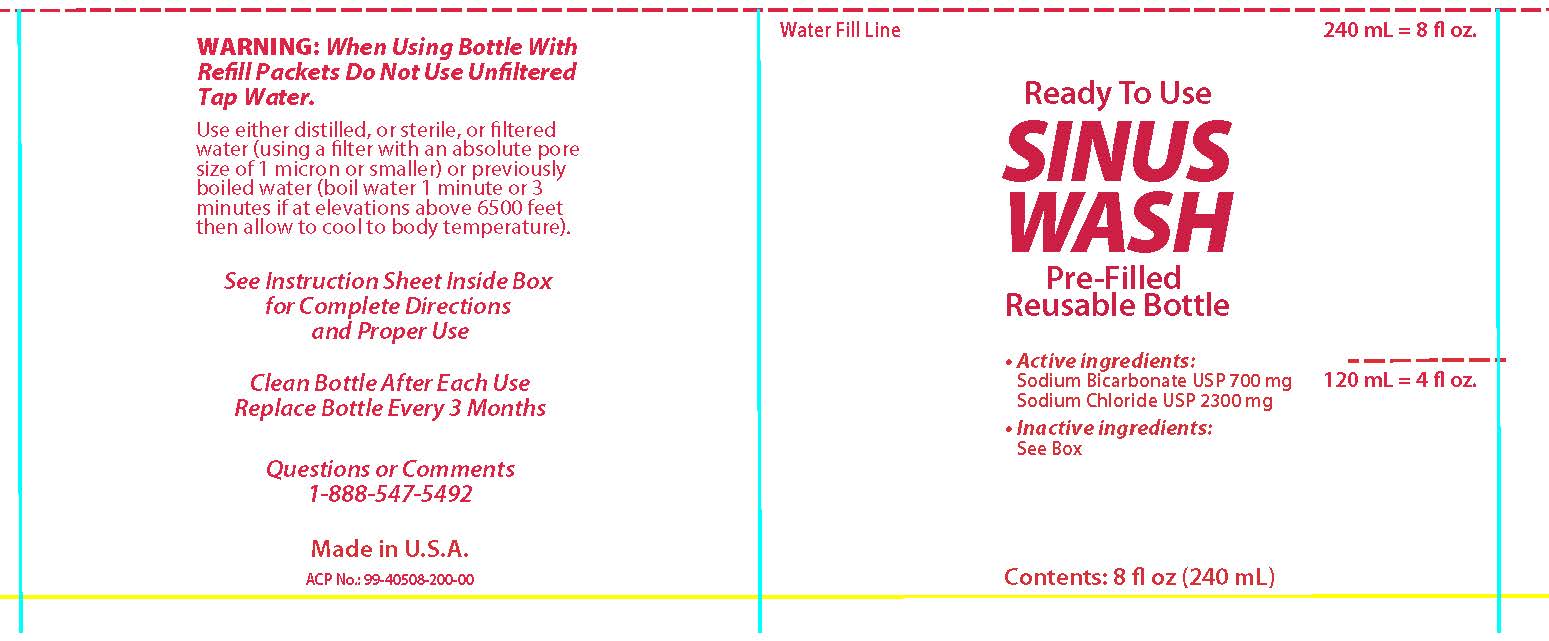 DRUG LABEL: CVS
NDC: 59779-865 | Form: SOLUTION
Manufacturer: CVS Pharmacy
Category: otc | Type: HUMAN OTC DRUG LABEL
Date: 20160315

ACTIVE INGREDIENTS: SODIUM BICARBONATE 22.2 mg/.1 g; SODIUM CHLORIDE 77.8 mg/.1 g
INACTIVE INGREDIENTS: WATER; BENZALKONIUM CHLORIDE

Active ingredients:

Sodium Bicarbonate USP 700 mg

Sodium Chloride USP 2300 mg

PURPOSE

Ready to Use

SINUS WASH

Inactive ingredients:

Purified Water ISP

Benzalkonium Chloride USP (Preservative)

WARNINGS

Warning: When Using Bottle With

Refill Packets Do Not Use Unfiltered

Tap Water.

Use either distilled, or sterile, or filered

water (using a filter with an absolute pore

size of 1 micron or smaller) or previously boiled

water (boil water 1 minute or 3 minutes

if at elevations above 6500 feet

then allow to cool to body temperature).

Questions or Comments

1-888-547-5492

DESCRIPTION

See Instruction Sheet Inside Box

for Complete Directions

and Proper Use

INSTRUCTIONS FOR USE

Sinus Wash

Pre-Filled Ready to Use

Saline Sinus Wash Kit

Instructions

DO NOT

SINUS WASH

WITH UNFILTERED

TAP WATER.

See important note*

for proper water

sources.

Read through entire instruction sheet

before using for the first time.

What is the Sinus Wash Kit?

The Sinus Wash Kit is an all natural

and medically proven method

for relieving allergies, nasal congestion, discomfort caused by dry air, sinus

infections, rhinitis of pregnancy and soothing irritated nasal passages. It

gently washes away mucus buildup from the nose and improves breathing.

Because it is gentle, it can be used up to every 2 hours as needed. Some

people use it as routinely as they brush their teeth while others use it only

on days when they need it.

* IMPORTANT NOTE

Do not sinus wash with unfiltered tap water. Use either distilled, or

sterile, or fi ltered (using a filter with an absolute pore size of 1 micron or

smaller) or previously boiled water (boil water 1 minute or 3 minutes if at

elevations above 6,500 feet, then allow to cool to body temperature).

Refill instructions for the Ready to Use

Sinus Wash Kit (with saline packets)

Read through entire section.

The Ready to Use Sinus Wash Kit can be used with the enclosed Saline

packets to make either an Isotonic or Hypertonic solution. Check with the

guide below or consult with your physician for best use.

An Isotonic solution creates a mild, less concentrated salt solution of 9 mg

of Sodium Chloride per mL of water, which has a similar salt concentration

of your body and may be more comfortable to use for some people initially

than a more concentrated Hypertonic solution.

A Hypertonic solution creates a higher, more concentrated salt solution

which is similar to the salt content of ocean water.

1. Wash your hands and make sure the bottle has been rinsed with water

that has been either distilled, sterilized, filtered or previously boiled.

2. Pour the pre-mixed saline dry ingredients into the Squeeze Bottle.

First-time users should start with 1 packet of the saline dry ingredients

to make an isotonic solution. As you become more accustomed to

the system, work up to using 2 full packets for a hypertonic solution.

Additional packets may be purchased from your nearest pharmacy.

3. Fill the bottle to the 8 oz line with proper water*.

4. Tighten the cap on the bottle securely, place one finger over the tip

of the cap and gently shake the bottle until the dry ingredients have

completely dissolved.

5. Lean over the sink with your head bent down so you are looking directly

into the basin. Place the tip of the cap up to the right nostril and gently

insert the tip so that it forms a comfortable seal. Aim the tip at the back

of your head, not at the top of your head. (continued on back)

Hints for a more comfortable nasal wash:

• Begin using the Sinus Wash System slowly – especially with children. A full

pot or bottle of solution on each side is not necessary to receive the full benefit.

• If the solution is too warm or too cold, the nasal wash will be uncomfortable.

• If stinging or irritation occurs, try using 1 packet of dry ingredients per

pot or bottle. Gradually work up to using the solution at full strength using 2

full packets per bottle. Do not use less than 1 packet.

• If you experience ear discomfort after use, try to blow your nose more gently

after the wash. If the problem persists, the openings of your Eustachian tubes

may be particularly wide and use of the system should be discontinued.

• Breathe continuously through the mouth when using the Sinus Wash System

to avoid solution draining from the back of the nose into the mouth.

• Some people experience irritation of the skin just inside the nostrils with

repeated nasal washing. Applying a thin layer of aloe to the inside of the

nostrils before or after the nasal wash will be soothing

KEEP OUT OF REACH OF CHILDREN

See Instruction Sheet Inside Box

DOSAGE AND ADMINISTRATION

See Instruction Sheet Inside Box

INDICATIONS AND USAGE

See Instruction Sheet Inside Box